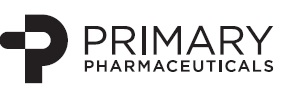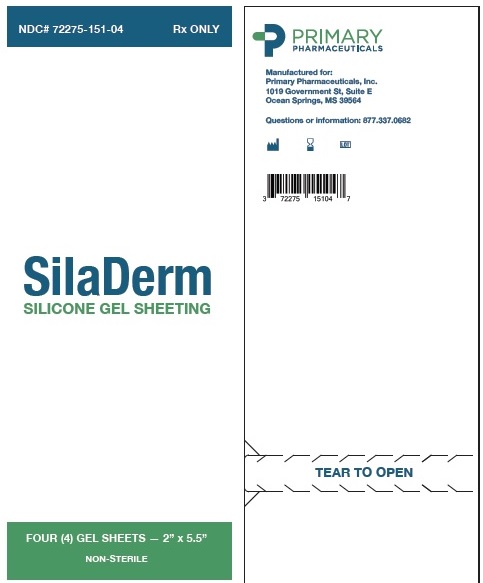 DRUG LABEL: Siladerm Fabric Silicone Gel Sheeting
NDC: 72275-151
Manufacturer: Primary Pharmaceuticals, Inc.
Category: other | Type: MEDICAL DEVICE
Date: 20201008

Siladerm Fabric Silicone Gel Sheeting

INDICATIONS

Siladerm Fabric Gel Sheeting is intended for use in the management, control and prevention of old and new hypertrophic or keloid scars resulting from burns or surgical or traumatic injury of the skin.

CONTRAINDICATIONS

Do not use on open wounds or when any Dermatological conditions disrupt the skin (such as a rash).

HOW SUPPLIED

Non-sterile product is labeled as such and supplied in a protective package within a protective outer container.

WARNINGS, PRECAUTIONS, ADVERSE REACTIONS

Possible complications include:

• Superficial maceration of the skin

• Rash

• Skin Discoloration

• Pruritus

• Sheeting tack and thickness vary

Rashes have been observed on skin under the fabric gel sheeting, this has been attributed to poor or insufficient hygiene. Similar rashes have been attributed to fabric gel sheeting being wrapped too tightly. Should a rash occur, stop using the fabric gel sheeting for 12 hours followed by using the fabric gel sheeting for 12 hours. If the rash persists, a physician should be contacted and fabric gel sheeting use should be discontinued.

Discoloration of the skin covered by Fabric Silicone Gel Sheeting has been reported, particularly in dark skinned patients. This effect appears to be transient, and may be similar to the discoloration experienced whenever an area of skin is covered for extended periods of time.

Some patients report differences in Fabric Gel sheeting surface tack and thickness from sheet to sheet. Perception of tack is subjective and the adhesive characteristic of Siladerm Fabric Gel Sheeting may vary. These variations do not affect the function of the product.

Small bubbles may form after repeated washing and use. This does not have an impact on the function of the product. Do not use creams, lotions, sun block or other silicone products on your skin when wearing fabric silicone gel sheeting. These products will create a barrier between the scar site and the fabric silicone gel, preventing a proper healing environment.

INSTRUCTIONS FOR USE

Siladerm Fabric Silicone Gel Sheeting

1. Wash both scar and hands per cleaning instructions.
2. Open the non-sterile pouch containing the Siladerm Fabric Silicone Gel Sheet.
3. The gel sheet is covered on “tacky” side by a plastic film. Remove the fabric gel sheeting from the plastic substrate liner prior to use.
4. The gel sheet may be cut into smaller pieces using scissors or a scalpel. Once you have determined the appropriate size of sheeting to use, apply tacky side to the scar. The gel sheeting should fully cover the scar and extend ¼ inch all the way around the scar border.
5. If the product is worn during sleep, it should be secured. Use of medical tape or other means is recommended to keep the product from falling off.

CLEANING INSTRUCTIONS

Remove the fabric gel sheet every 12 hours to wash both the scar and the gel sheet. In a basin of warm water, work up a small amount of lather with soap. Gently wash the piece of gel sheeting in the soapy water, rinse, and then air dry. Make sure the sheeting is completely dry before re-applying to the scar. After washing, rinsing and drying the scar site re-apply the piece of gel sheeting.

WEARING TIME

Optimal wearing time for Siladerm Fabric Silicone Gel Sheeting is 24 hours per day. If it is not possible to wear the gel sheet for the recommended 24 hour period, a minimum of 12 hours per day is required, washing per the instructions above once in that period. Follow this procedure each day, washing and re-applying the gel sheeting to the scar for 1 to 2 weeks. At that time the piece of gel sheeting will begin to lose its adhesive quality and/or may become embedded with surface dirt. When this occurs, discard the piece of gel sheeting and apply a new piece.

The overall optimal period of use is usually 8 to 12 weeks.

Manufactured for:
Primary Pharmaceuticals, Inc.
1019 Government St, Suite E
Ocean Springs, MS 39564

Questions or information: 877.337.0682